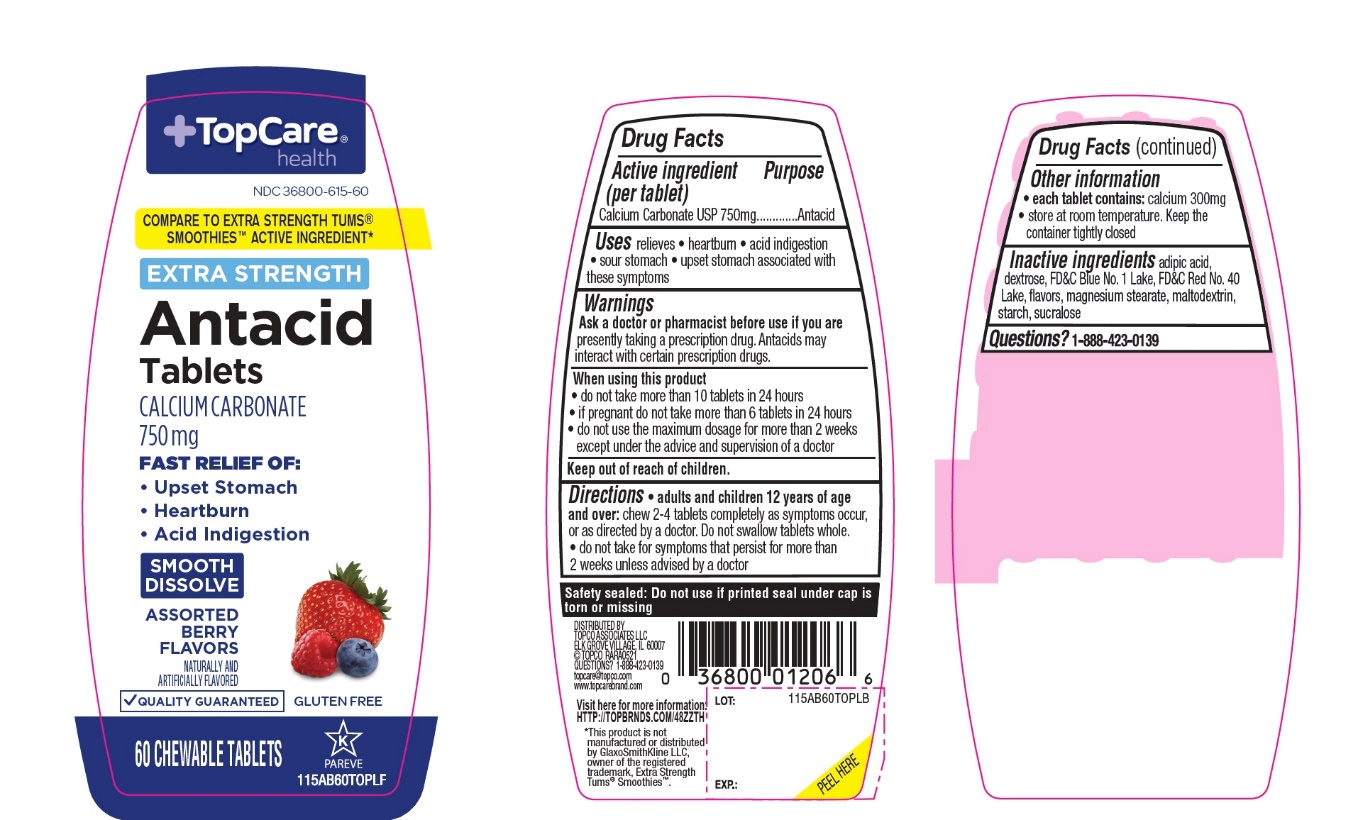 DRUG LABEL: Topcare Antacid Extra Strength

NDC: 36800-615 | Form: TABLET, CHEWABLE
Manufacturer: Topco Associates LLC
Category: otc | Type: HUMAN OTC DRUG LABEL
Date: 20251110

ACTIVE INGREDIENTS: CALCIUM CARBONATE 750 mg/1 1
INACTIVE INGREDIENTS: ADIPIC ACID; DEXTROSE, UNSPECIFIED FORM; FD&C BLUE NO. 1; FD&C RED NO. 40; MAGNESIUM STEARATE; MALTODEXTRIN; STARCH, CORN; SUCRALOSE

Topco Associates LLC. 60 Chewable Tablets Antacid Drug Facts

Active ingredient (per tablet)

Calcium Carbonate USP 750mg

Purpose

Antacid

Uses

relieves

- heartburn
- acid indigestion
- sour stomach
- upset stomach associated with these symptoms

Ask a doctor or pharmacist before use if you are

presently taking a prescription drug. Antacids may interact with certain prescription drugs.

When using this product

- do not take more than 10 tablets in 24 hours
- if pregnant do not take more than 6 tablets in 24 hours
- do not use the maximum dosage for more than 2 weeks except under the advice and supervision of a doctor

Directions

- adults and children 12 years of age and over:chew 2-4 tablets as symptoms occur, or as directed by a doctor. Do not swallow tablets whole.
- do not take for symptoms that persist for more than 2 weeks unless advised by a doctor

Other information

- each tablet contains:elemental calcium 300mg
- store at room temperature. Keep the container tightly closed.

Inactive ingredients

adipic acid, dextrose, FD&C Blue No. 1, FD&C Red No. 40, flavors, magnesium stearate, maltodextrin, starch, sucralose

Questions?

1-888-423-0139

Principal Display Panel

+TopCare®health™

NDC#36800-615-60

COMPARE TO EXTRA STRENGTH TUMS® SMOOTHIES ACTIVE INGREDIENT*

EXTRA STRENGTH

Antacid Tablets

CALCIUM CARBONATE 750 mg

OUR PHARMACISTS RECOMMEND

FAST RELIEF OF:

- Upset Stomach
- Heartburn
- Acid Indigestion

SMOOTH DISSOLVE

ASSORTED BERRY FLAVORS

- QUALITY GUARANTEED

GLUTEN FREE

60 CHEWABLE TABLETS

K PAREVE

DISTRIBUTED BY

TOPCO ASSOCIATES LLC

ELK GROVE VILLAGE, IL 60007

©TOPCO RARA0918

QUESTIONS? 1-888-423-0139

topcare@topco.comwww.topcarebrand.com

Visit here for more information: http://topbrnds.com/48ZS256

*This product is not manufactured or distributed by GlaxoSmithKline, the distributor of Extra Strength Tums®Smoothies.